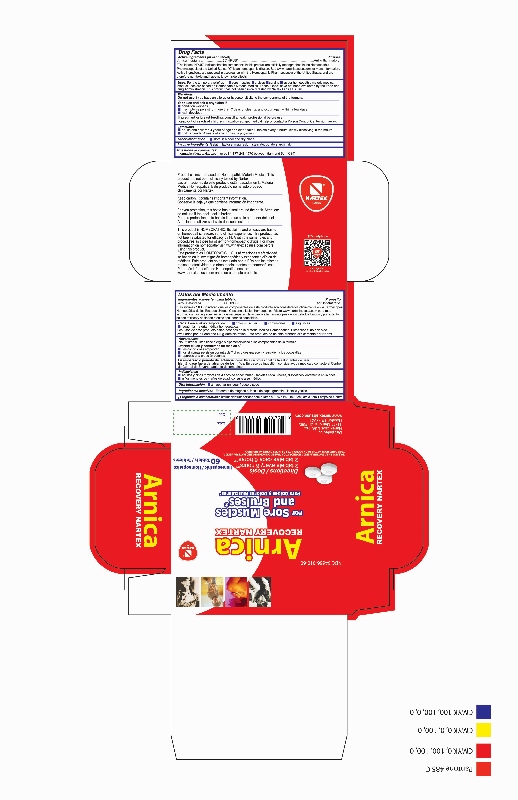 DRUG LABEL: Arnica Recovery
NDC: 34666-010 | Form: TABLET
Manufacturer: NARTEX LABORATORIOS HOMEOPATICOS SA DE CV
Category: homeopathic | Type: HUMAN OTC DRUG LABEL
Date: 20180227

ACTIVE INGREDIENTS: ARNICA MONTANA 6 [hp_C]/1 1
INACTIVE INGREDIENTS: GELATIN; LACTOSE; MAGNESIUM STEARATE; STARCH, POTATO; TALC

ACTIVE INGREDIENT

Arnica montana 6C HPUS

PURPOSE

Arnica montana.......6C HPUS*..........Anti-inflammatory

*The letters "HPUS" indicate that the components in this product are officially monographed in the Homeopathic Pharmacopoeia of the United States. C is a homeopathic dilution. See www.nartexlabsusa.com for more information. Active ingredients are preparaed in accordance with the Homeopathic Pharmacopoeia of the United States, and are therefore non-toxic and have no known side effects.

INDICATIONS AND USAGE

For the temporary relief of

- sore muscles
- bruises
- sprains

as per homeopathic materia medica

Product uses are based on Homeopathic Materia Medica. These "Uses" have not been evaluated by teh Food and Drug Administration. This product has not been clinically tested by Nartex Labs USA, Inc.

Do not use if you have an allergy or hypersensitivity to the components of the formula.

Stop and ask a physician if:

- condition worsens
- if symptoms persist for more than 7 days or clear up and occur again within a few days
- rash develops

PREGNANCY OR BREAST FEEDING

If pregnant or breast feeding, consult a health professional before use.

Keep out of reach of children. If swallowed, get medical help or contact a Poison Control Center right away.

Directions:

- adults and children 4 years of age and older: take 2 tablets every 6 hours, slowly dissolving in mouth
- children under 4 years of age: consult a physician

STORAGE AND HANDLING

store in a cool and dry place

INACTIVE INGREDIENT

Gelatin, lactose, magnesium stearate, potato starch, talc

Questions or comments? informacion@nartexlabs.com or call 1-877-248-1970 between 9am and 5pm CST

DESCRIPTION

Distributed by:

Nartex Labs USA, Inc.

11711 Memorial Dr. #685

Houston TX 77024

www.nartexlabsusa.com

DESCRIPTION

Product claims are based on Homeopathic Materia Medica. This product has not been clinically tested by Nartex.

Keep carton. It contains important information.

For you protection, this bottle has a seal around the neck. Attention: do not use if hte neck seal is broken.

This product is HOMEOPATHIC. Its claim and efficacy are based on homeopathic research and clinical experience. This product has not been evaluated for efficacy by FDA with the same rules and procedures as those for other non-homeopathic drugs. For more information on homeopathy visit www.nartexlabsusa.com before using this product.

PACKAGE LABEL

NDC 34666-010-60

Arnica

Recovery Nartex

For Sore Muscles and Bruises*

Directions

2 tablets every 6 hours**

Homeopathic

60 Tablets

*Based on Homeopathic Materia Medica

**See directions at the Back.